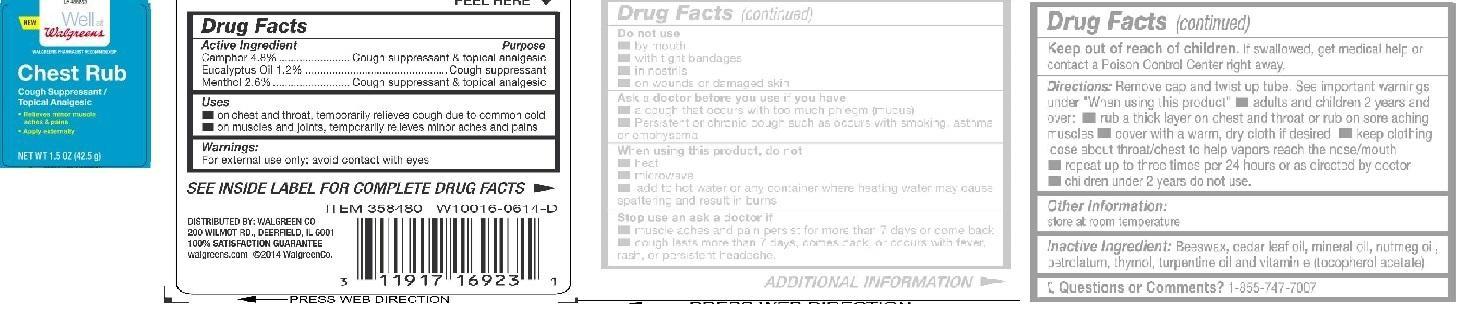 DRUG LABEL: Chest Rub
NDC: 0363-8480 | Form: LOTION
Manufacturer: Walgreens Company
Category: otc | Type: HUMAN OTC DRUG LABEL
Date: 20140716

ACTIVE INGREDIENTS: CAMPHOR (NATURAL) 4.8 kg/42.5 g; EUCALYPTUS OIL 1.2 kg/42.5 g; MENTHOL 2.6 kg/42.5 g
INACTIVE INGREDIENTS: YELLOW WAX; CEDAR LEAF OIL; MINERAL OIL; NUTMEG OIL; PETROLATUM; THYMOL; TURPENTINE OIL; .ALPHA.-TOCOPHEROL ACETATE

Chest Rub
Drug Facts

Active Ingredient

Camphor 4.8%

Eucalyptus Oil 1.2%

Menthol 2.6%

Purpose

Cough suppressant & topical analgesic

Cough suppressant

Cough suppressant & topical analgesic

Uses

- on chest and throat, temporarily relieves cough due to common cold
- on muscles and joints, temporarily relieves minor aches and pains

Warnings:

For external use only; avoid contact with eyes

Do not use

- by mouth
- with tight bandages
- in nostrils
- on wounds or damaged skin

Ask a doctor before you use if you have

- a cough that occurs with too much phlegm (mucus)
- Persistent or chronic cough such as occurs with smoking, asthma or emphysema

When using this product, do not

- heat
- microwave
- add to hot water or any container where heating water may cause spattering and results in burns

Stop use and ask a doctor if

- muscle aches and pain persist for more that 7 days or come back
- cough lasts more that 7 days, comes back, or occurs with fever, rash or persistent headache.

Keep out of reach of children. If swallowed, get medical help or contact a Poison Control Center right away.

DOSAGE AND ADMINISTRATION

Directions: Remove cap and twist up tube. See important warnings under "When using this product"

- adults and children 2 years and over:
- rub a thick layer on chest and throat or rub on sore aching muscles
- cover with a warm, dry cloth if desired
- keep clothing loose about throat/chest to help vapors reach the nose/mouth
- repeat up three times per 24 hours or as directed by doctor
- children under 2 years do not ues.

Other Information:

store at room temperature

Inactive Ingredient:

Beeswax, cedar leaf oil, mineral oil, nutmeg oil, petrolatum, thymol, turpentine oil and vitamin e (tocopherol acetate)

Questions or Comments?

1-855-747-7007

Distributed by: Walgreen Co

200 Wilmot Rd., Deerfield, IL 6001

100% Satisfaction Guarantee

Walgreens.com ©2014 Walgreen Co.

Prinicipal Display Panel

Chest Rub

Cough Suppressant/

Topical Analgesic